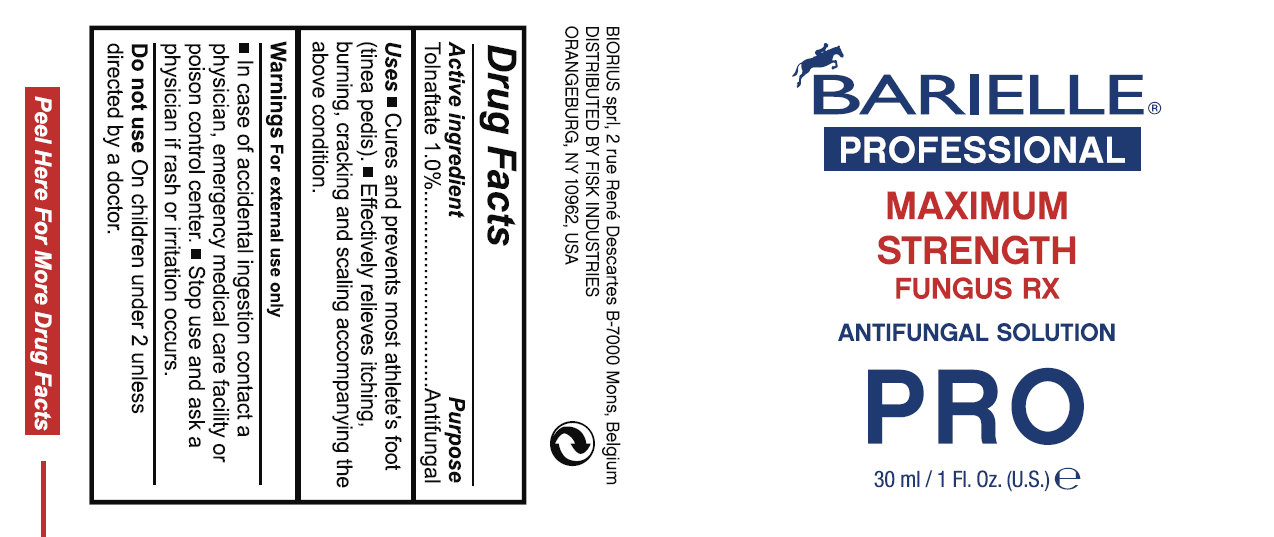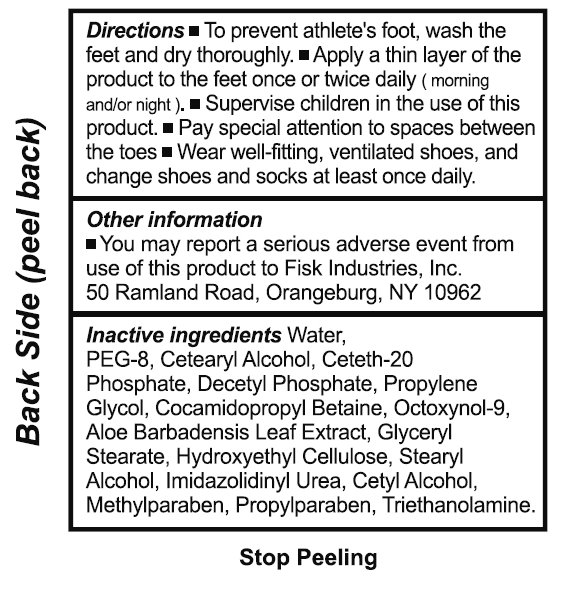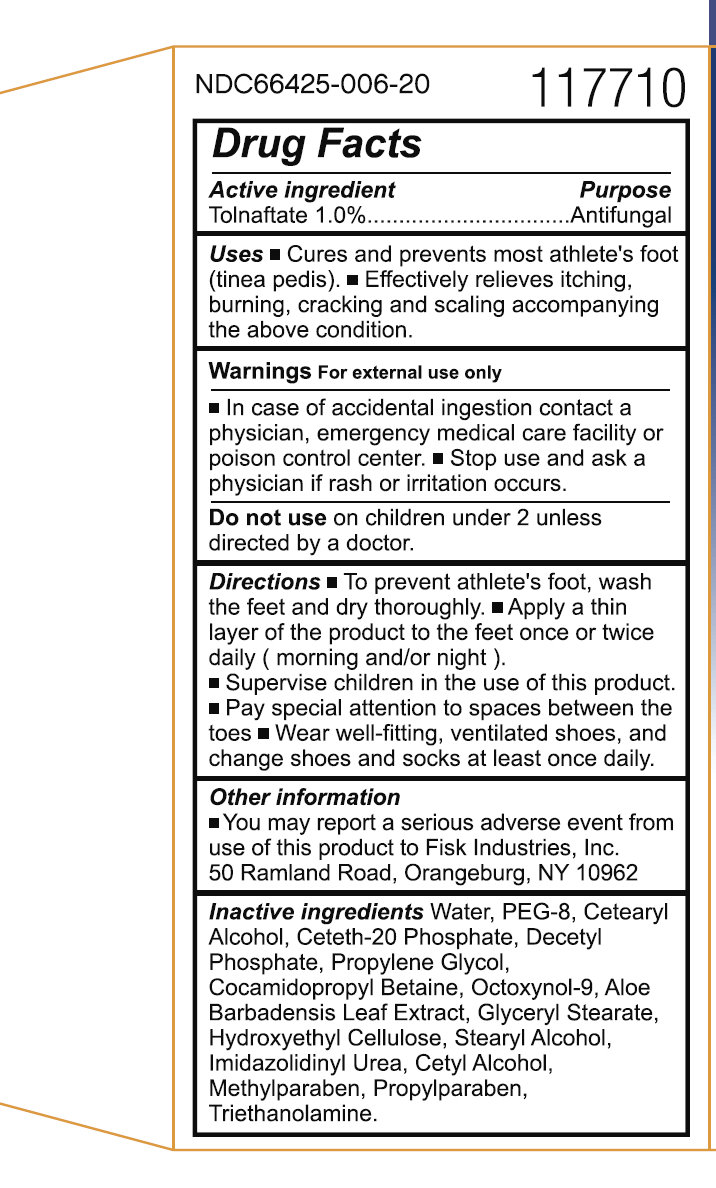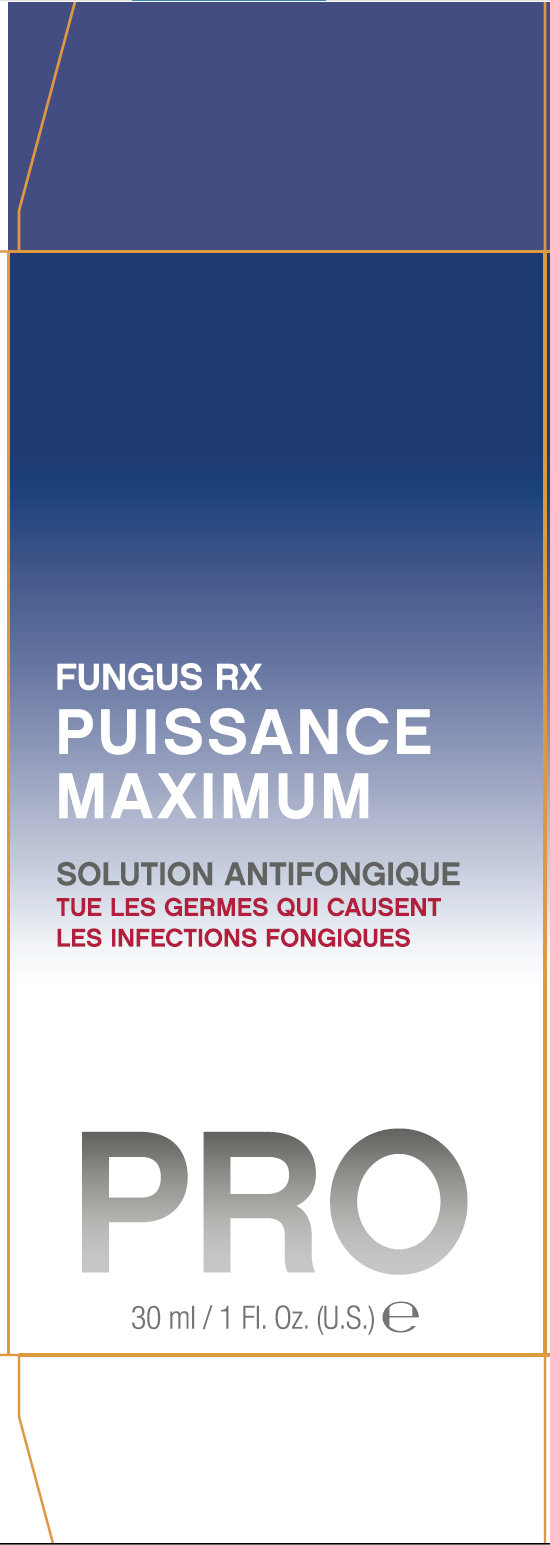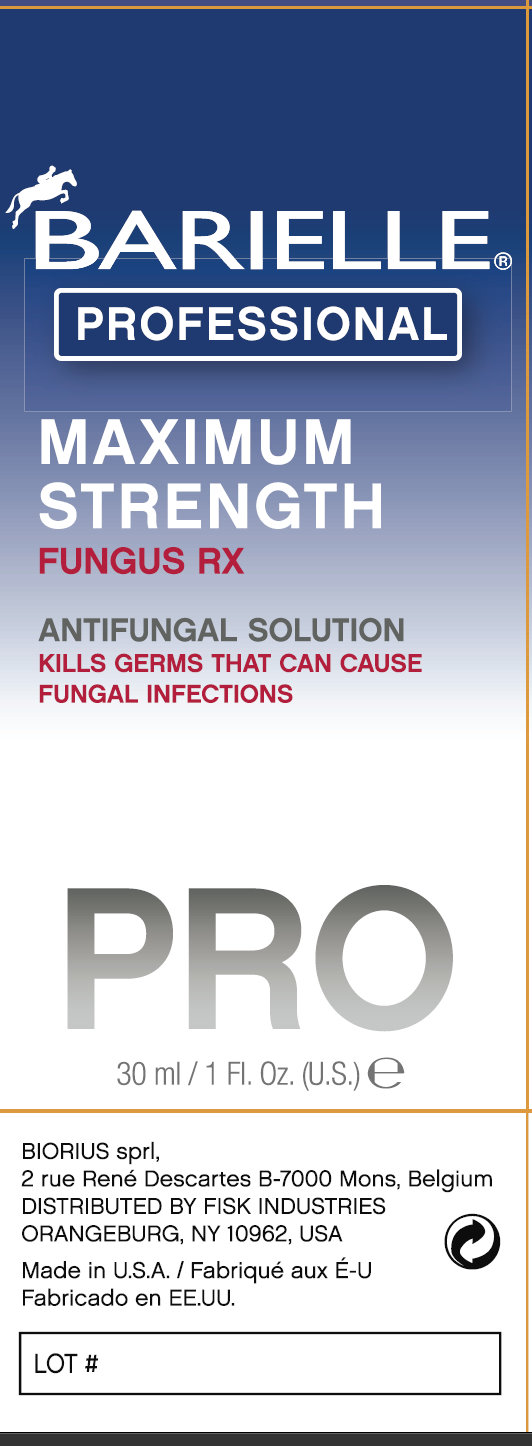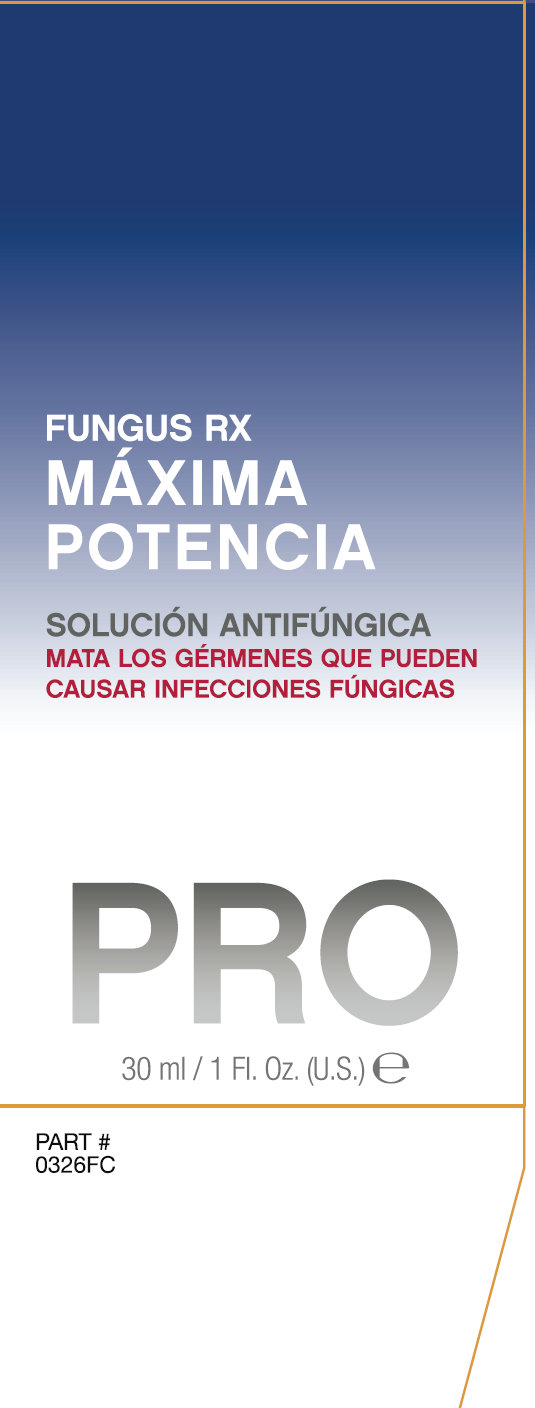 DRUG LABEL: Barielle Professional Maximum Strength Fungus Rx Antifungal PRO
NDC: 42593-001 | Form: SOLUTION
Manufacturer: Fisk Industries
Category: otc | Type: HUMAN OTC DRUG LABEL
Date: 20120202

ACTIVE INGREDIENTS: TOLNAFTATE 1.0 mL/100 mL
INACTIVE INGREDIENTS: WATER; POLYETHYLENE GLYCOL 400; CETOSTEARYL ALCOHOL; CETETH-20; PROPYLENE GLYCOL; COCAMIDOPROPYL BETAINE; OCTOXYNOL 9; ALOE VERA LEAF; GLYCERYL MONOSTEARATE; STEARYL ALCOHOL; IMIDUREA; CETYL ALCOHOL; METHYLPARABEN; PROPYLPARABEN; TROLAMINE

Barielle Professional Maximum Strength Fungus Rx Antifungal Solution PRO

Active ingredient

Active ingredient Purpose
Tolnaftate 1.0%.................................Antifungal

Uses

- Cures and prevents most athlete's foot (tinea pedis). - Effectively relieves itching, burning, cracking and scaling accompanying the above condition.

Warnings

For external use only

Keep out of reach of children

- In case of accidental ingestion contact a physician, emergency medical care facility or poison control center.

Stop use

- Stop use and ask a physician if rash or irritation occurs.

Do not use

On children under 2 unless directed by a doctor.

Directions

- To prevent athlete's foot, wash the feet and dry thoroughly. - Apply a thin layer of the product to the feet once or twice daily (morning and/or night). - Supervise children in the use of this product. - Pay special attention to spaces between the toes - Wear well-fitting, ventilated shoes, and change shoes and socks at least once daily.

Other information

- You may report a serious adverse event from use of this product to Fisk Industries, Inc. 50 Ramland Road, Orangeburg, NY 10962

Inactive ingredients

Water, PEG-8, Cetearyl Alcohol, Ceteth-20 Phosphate, Decetyl Phosphate, Propylene Glycol, Cocamidopropyl Betaine, Octoxynol-9, Aloe Barbadensis Leaf Extract, Glyceryl Stearate, Hydroxyethyl Cellulose, Stearyl Alcohol, Imidazolidinyl Urea, Cetyl Alcohol, Methylparaben, Propylparaben, Triethanolamine.

Purpose

Antifungal

Description

NDC66425-006-20 117710
BIORIUS sprl, 2 rue René Descartes B-7000 Mons, Belgium DISTRIBUTED BY FISK INDUSTRIES ORANGEBURG, NY 10962, USA Made in U.S.A. LOT # 0326BR 7 20817 30326 1 PART # 0326FC

PACKAGE LABEL

BARIELLE PROFESSIONAL MAXIMUM STRENTH FUNGUS RX ANTIFUNGAL SOLUTION PRO 30 ml / Fl. Oz. (U.S.) e

Directions

PACKAGE LABEL

NDC66425-006-20 117710 Drug Facts

PACKAGE LABEL

FUNGUS RX PUISSANCE MAXIMUM SOLUTION ANTIFONGIQUE TUE LES GERMES QUI CAUSENT LES INFECTIONS FONGIQUES PRO 30 ml / Fl. Oz. (U.S.) e

PACKAGE LABEL

BARIELLE PROFESSIONAL MAXIMUM STRENGTH FUNGUS RX ANTIFUNGAL SOLUTION KILLS GERMS THAT CAN CAUSE FUNGAL INFECTIONS PRO 30 ml / Fl. Oz. (U.S.) e BIORIUS sprl, 2 rue René Descartes B-7000 Mons, Belgium DISTRIBUTED BY FISK INDUSTRIES ORANGEBURG, NY 10962, USA Made in U.S.A. LOT #

PACKAGE LABEL

FUNGUS RX MAXIMA POTENCIA SOLUCION ANTIFUNGICA MATA LOS GERMENES QUE PUEDEN CAUSAR INFECCIONES FUNGICAS PRO 30 ml / Fl. Oz. (U.S.) e PART # 0326FC